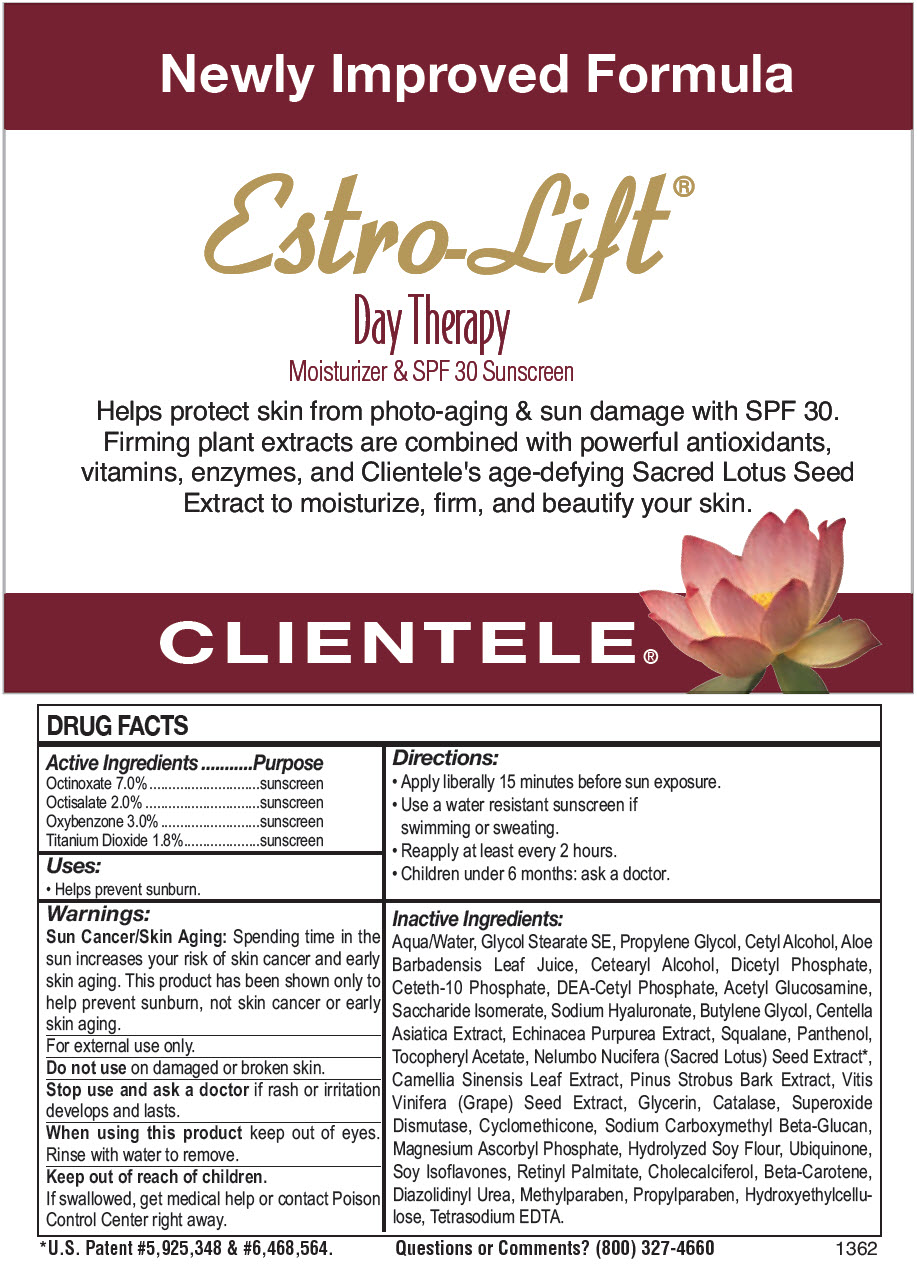 DRUG LABEL: Estro-Lift Day Therapy 
NDC: 64483-378 | Form: CREAM
Manufacturer: Clientele, Inc.
Category: otc | Type: HUMAN OTC DRUG LABEL
Date: 20191210

ACTIVE INGREDIENTS: Octinoxate 7000 mg/1000 g; Octisalate 2000 mg/1000 g; Oxybenzone 3000 mg/1000 g; Titanium Dioxide 1600 mg/1000 g
INACTIVE INGREDIENTS: Water; Glycol Stearate SE; PPG-30 CETYL ETHER; Cetyl Alcohol; ALOE VERA LEAF; CETOSTEARYL ALCOHOL; DIHEXADECYL PHOSPHATE; Ceteth-10 Phosphate; DIETHANOLAMINE CETYL PHOSPHATE; DISODIUM ACETYL GLUCOSAMINE PHOSPHATE; Saccharide Isomerate; HYALURONATE SODIUM; Butylene Glycol; Centella Asiatica; Echinacea Purpurea; Squalane; Panthenol; .ALPHA.-TOCOPHEROL ACETATE; NELUMBO NUCIFERA SEED; GREEN TEA LEAF; PINUS STROBUS BARK; VITIS VINIFERA SEED; Glycerin; CATALASE (BOS TAURUS); SUPEROXIDE DISMUTASE (SACCHAROMYCES CEREVISIAE); Cyclomethicone; SODIUM CARBOXYMETHYL .BETA.-GLUCAN (DS 0.65-0.85); Magnesium Ascorbyl Phosphate; SOYBEAN; UBIDECARENONE; Soy Isoflavones; VITAMIN A PALMITATE; Cholecalciferol; BETA CAROTENE; Methylparaben; Propylparaben; HYDROXYETHYL ETHYLCELLULOSE; EDETATE SODIUM; Diazolidinyl Urea

Estro-Lift® Day Therapy
Moisturizer & SPF 30 Sunscreen

DRUG FACTS

ACTIVE INGREDIENT

Active Ingredients | Purpose
Octinoxate 7.0% | sunscreen
Octisalate 2.0% | sunscreen
Oxybenzone 3.0% | sunscreen
Titanium Dioxide 1.8% | sunscreen

Uses

- Helps prevent sunburn.

Warnings

Sun Cancer/Skin Aging

Spending time in the sun increases your risk of skin cancer and early skin aging. This product has been shown only to help prevent sunburn, not skin cancer or early skin aging.

For external use only.

Do not use on damaged or broken skin.

Stop use and ask a doctor if rash or irritation develops and lasts.

When using this product keep out of eyes. Rinse with water to remove.

Keep out of reach of children.

If swallowed, get medical help or contact Poison Control Center right away.

Directions

- Apply liberally 15 minutes before sun exposure.
- Use a water resistant sunscreen if swimming or sweating.
- Reapply at least every 2 hours.
- Children under 6 months: ask a doctor.

Inactive Ingredients

Aqua/Water, Glycol Stearate SE, Propylene Glycol, Cetyl Alcohol, Aloe Barbadensis Leaf Juice, Cetearyl Alcohol, Dicetyl Phosphate, Ceteth-10 Phosphate, DEA-Cetyl Phosphate, Acetyl Glucosamine, Saccharide Isomerate, Sodium Hyaluronate, Butylene Glycol, Centella Asiatica Extract, Echinacea Purpurea Extract, Squalane, Panthenol, Tocopheryl Acetate, Nelumbo Nucifera (Sacred Lotus) Seed Extract [U.S. Patent #5,925,348 & #6,468,564.] , Camellia Sinensis Leaf Extract, Pinus Strobus Bark Extract, Vitis Vinifera (Grape) Seed Extract, Glycerin, Catalase, Superoxide Dismutase, Cyclomethicone, Sodium Carboxymethyl Beta-Glucan, Magnesium Ascorbyl Phosphate, Hydrolyzed Soy Flour, Ubiquinone, Soy Isoflavones, Retinyl Palmitate, Cholecalciferol, Beta-Carotene, Diazolidinyl Urea, Methylparaben, Propylparaben, Hydroxyethylcellulose, Tetrasodium EDTA.

Questions or Comments?

(800) 327-4660

PRINCIPAL DISPLAY PANEL - 34 g Jar Label

Newly Improved Formula

Estro-Lift®

Day Therapy
Moisturizer & SPF 30 Sunscreen

Helps protect skin from photo-aging & sun damage with SPF 30.
Firming plant extracts are combined with powerful antioxidants,
vitamins, enzymes, and Clientele's age-defying Sacred Lotus Seed
Extract to moisturize, firm, and beautify your skin.

CLIENTELE®